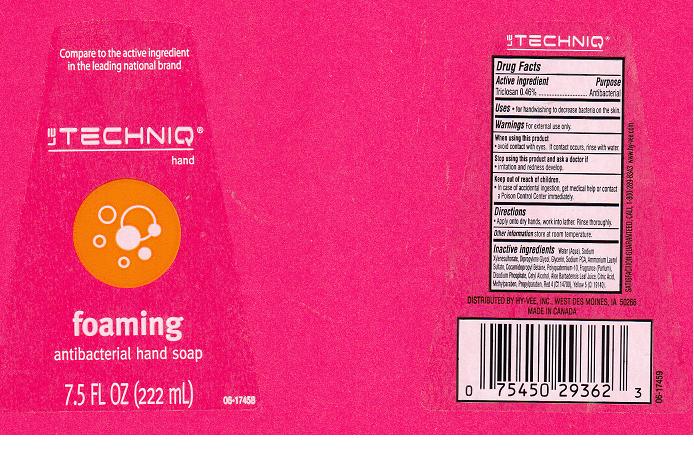 DRUG LABEL: ANTIBACTERIAL
NDC: 42507-177 | Form: SOLUTION
Manufacturer: HYVEE INC
Category: otc | Type: HUMAN OTC DRUG LABEL
Date: 20110804

ACTIVE INGREDIENTS: TRICLOSAN 0.46 mL/100 mL
INACTIVE INGREDIENTS: WATER; SODIUM XYLENESULFONATE; DIPROPYLENE GLYCOL; GLYCERIN; SODIUM PYRROLIDONE CARBOXYLATE; AMMONIUM LAURYL SULFATE; COCAMIDOPROPYL BETAINE; POLYQUATERNIUM-10 (400 CPS AT 2%); SODIUM PHOSPHATE, DIBASIC; CETYL ALCOHOL; ALOE VERA LEAF; CITRIC ACID MONOHYDRATE; METHYLPARABEN; PROPYLPARABEN; FD&C RED NO. 4; FD&C YELLOW NO. 5

DRUG FACTS BOX

ACTIVE INGREDIENT

TRICLOSAN 0.46%

PURPOSE

ANTIBACTERIAL

USES

FOR HAND WASHING TO DECREASE BACTERIA ON THE SKIN

WARNINGS

FOR EXTERNAL USE ONLY

WHEN USING THIS PRODUCT

AVOID CONTACT WITH EYES. IF CONTACT OCCURS, RINSE WITH WATER.

STOP USING THIS PRODUCT AND ASK DOCTOR IF

IF IRRITATION AND REDNESS DEVELOP

KEEP OUT OF REACH OF CHILDREN

IN CASE OF ACCIDENTAL INGESTION, GET MEDICAL HELP OR CONTACT A POISON CONTROL IMMEDIATELY

DIRECTIONS

APPLY ONTO DRY HANDS, WORK INTO LATHER. RINSE THOROUGHLY.

OTHER INFORMATION

STORE AT ROOM TEMPERATURE

INACTIVE INGREDIENTS

WATER (AQUA), SODIUM XYLENE SULFONATE, DIPROPYLENE GLYCOL, GLYCERIN, SODIUM PCA, AMMONIUM LAURYL SULFATE, COCAMIDOPROPYL BETAINE, POLYQUATERNIUM-10, FRAGRANCE (PARFUM), DISODIUM PHOSPHATE, CETYL ALCOHOL, ALOE BARBADENSIS LEAF JUICE, CITRIC ACID, METHYLPARABEN, PROPYLPARABEN, RED 4 (CI 14700), YELLOW 5 (CI 19140)

LABEL COPY

Enter section text here